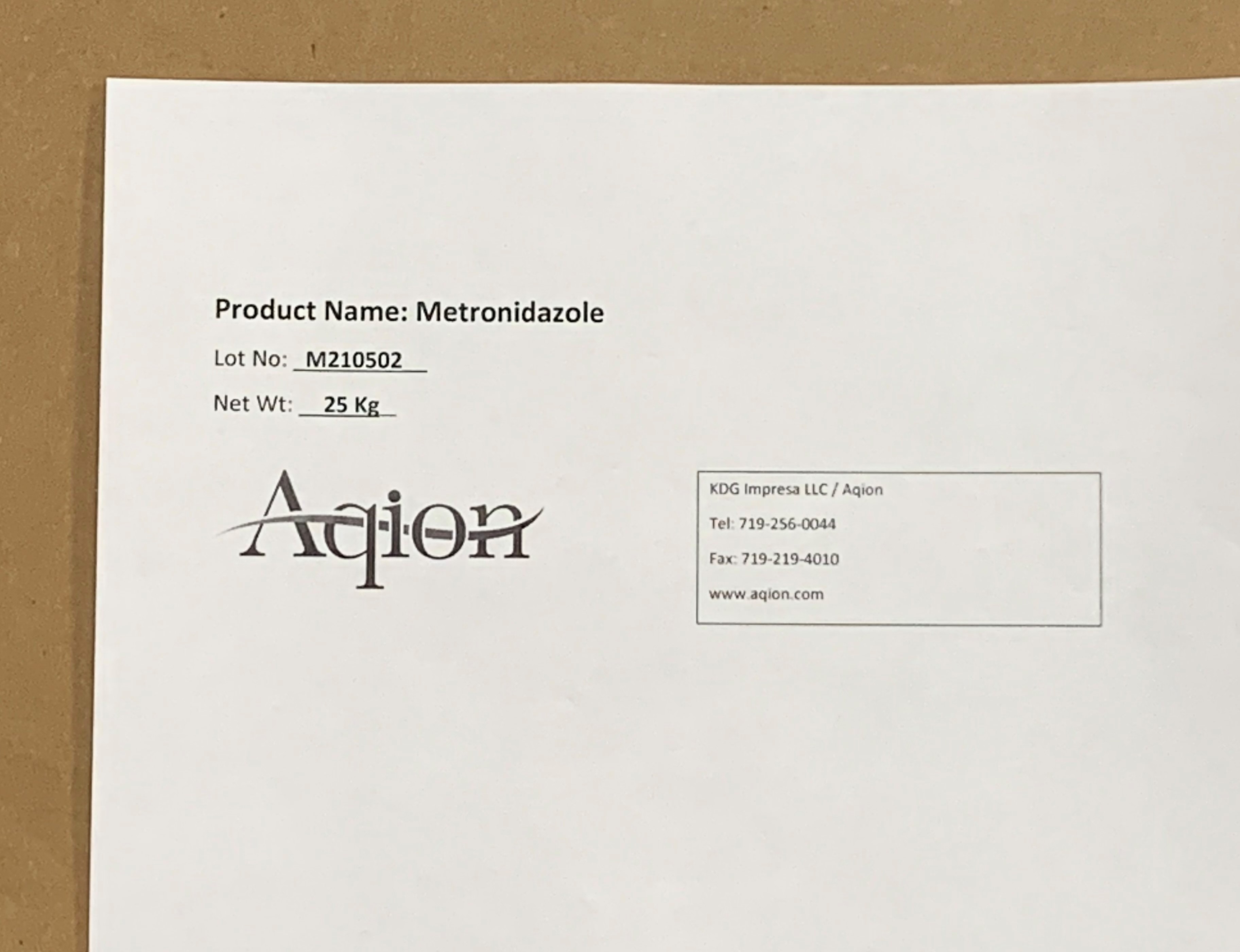 DRUG LABEL: Metronidazole
NDC: 43457-537 | Form: POWDER
Manufacturer: KDG Impresa LLC, Aqion
Category: other | Type: BULK INGREDIENT - ANIMAL DRUG
Date: 20220221

ACTIVE INGREDIENTS: METRONIDAZOLE 1 kg/1 kg

Metronidazole